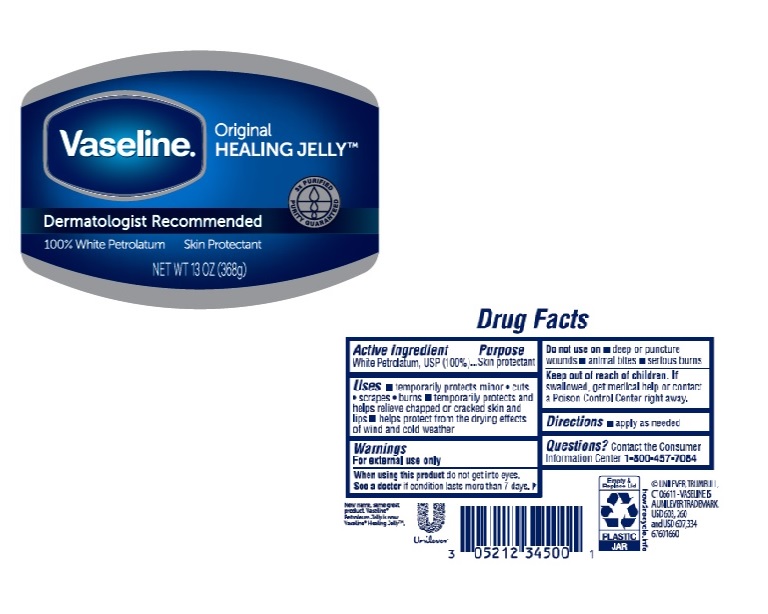 DRUG LABEL: Vaseline
NDC: 64942-1874 | Form: JELLY
Manufacturer: Conopco Inc. d/b/a Unilever
Category: otc | Type: HUMAN OTC DRUG LABEL
Date: 20241107

ACTIVE INGREDIENTS: PETROLATUM 99.96 g/100 g
INACTIVE INGREDIENTS: WATER

Vaseline Healing Jelly

Active ingredient

WHITE PETROLATUM, USP (100%)

Purpose

skin protectant

Uses

temporarily protects minor

- cuts
- scrapes
- burns

temporarily protects and helps relieve chapped or cracked skin and lips

helps protect from the drying effects of wind and cold weather

Warnings

For external use only
When using this product do not get into eyes
See a doctor if condition last more than 7 days
Do not use on

- deep or puncture wounds
- animal bites
- serious burns

Keep out of reach of children
If swallowed get medical help or contact a Poison Control Center right away.

Directions

apply as needed

Inactive Ingredient

Water

Questions?

Call 1-800-457-7084